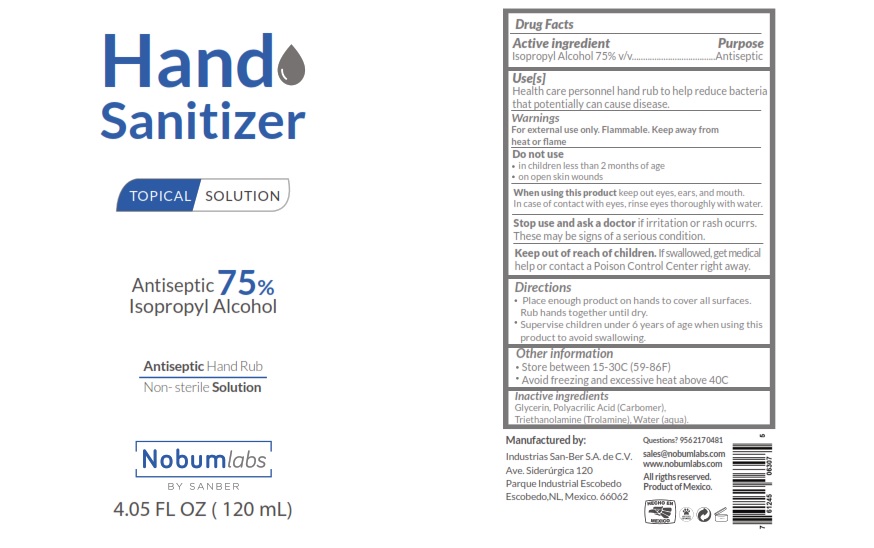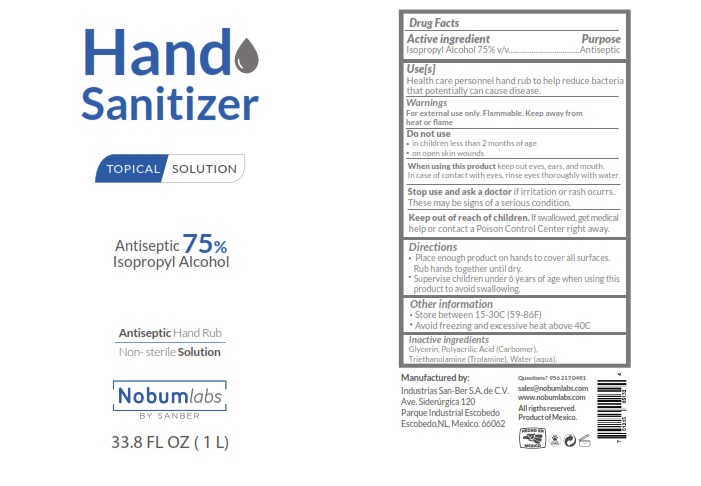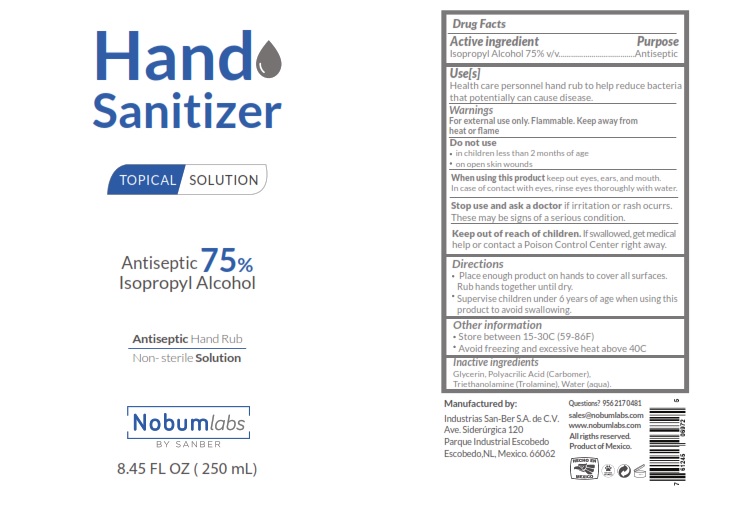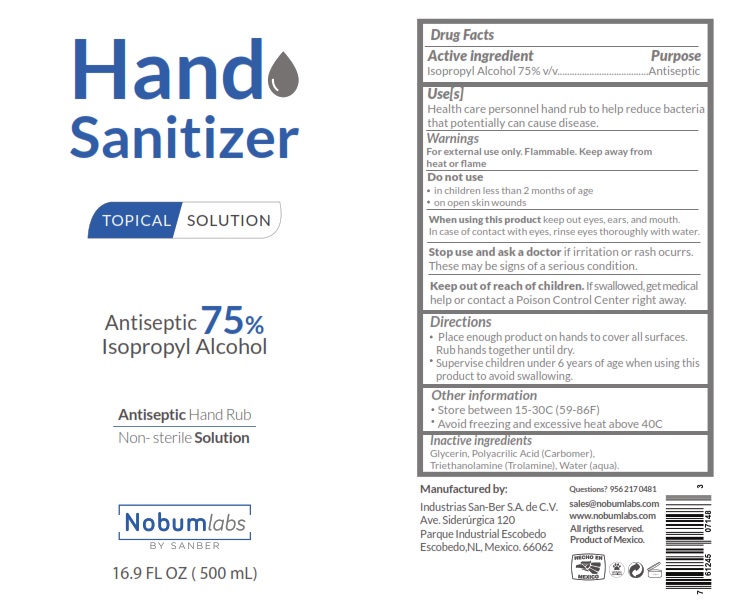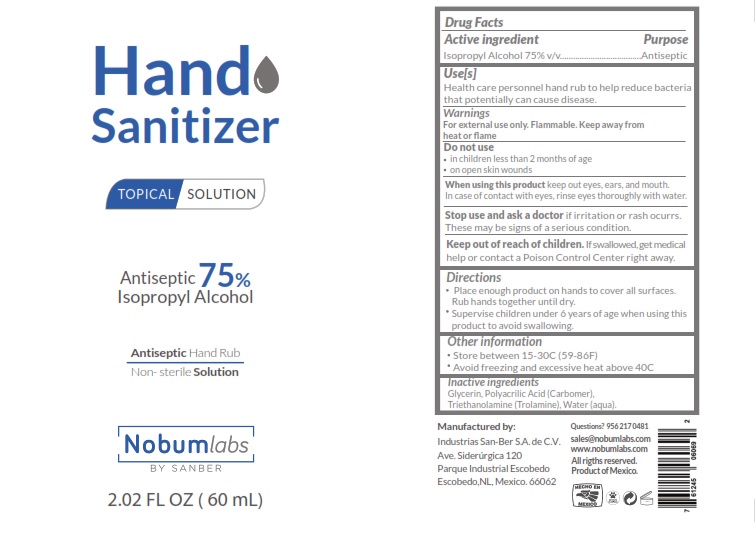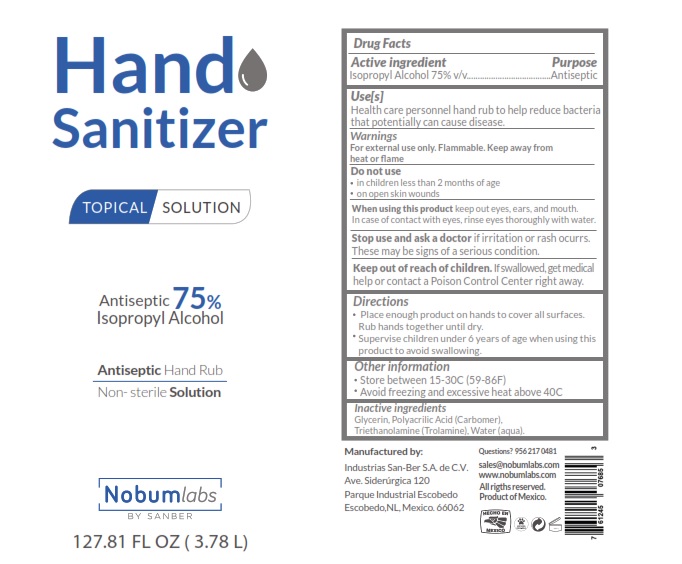 DRUG LABEL: Hand Sanitizer
NDC: 78755-002 | Form: GEL
Manufacturer: Industrias San-Ber, S.A. de C.V.
Category: otc | Type: HUMAN OTC DRUG LABEL
Date: 20220127

ACTIVE INGREDIENTS: ISOPROPYL ALCOHOL 75 mL/100 mL
INACTIVE INGREDIENTS: GLYCERIN 1 mL/100 mL; POLYACRYLIC ACID (8000 MW) 0.5 mL/100 mL; WATER 23.1 mL/100 mL; TROLAMINE 0.4 mL/100 mL

Active Ingredient(s)

Isopropyl Alcohol 75% v/v. Purpose: Antiseptic

Purpose

Antiseptic, Hand Sanitizer

Use

Hand Sanitizer to help reduce bacteria that potentially can cause disease. For use when soap and water are not available.

Warnings

For external use only. Flammable. Keep away from heat or flame

Do not use

- in children less than 2 months of age
- on open skin wounds

When using this product keep out of eyes, ears, and mouth. In case of contact with eyes, rinse eyes thoroughly with water.
Stop use and ask a doctor if irritation or rash occurs. These may be signs of a serious condition.
Keep out of reach of children. If swallowed, get medical help or contact a Poison Control Center right away.

Stop use and ask a doctor if irritation or rash occurs. These may be signs of a serious condition.

Keep out of reach of children. If swallowed, get medical help or contact a Poison Control Center right away.

Directions

- Place enough product on hands to cover all surfaces. Rub hands together until dry.
- Supervise children under 6 years of age when using this product to avoid swallowing.

Other information

- Store between 15-30C (59-86F)
- Avoid freezing and excessive heat above 40C (104F)

Inactive ingredients

Glycerin, polyacrylic acid (Carbomer), triethanolamine (Trolamine), Water (aqua)

Package Label - Principal Display Panel

60mL NDC: 78755-002-01

Package Label- Principal Display Panel

120 mL NDC: 78755-002-02

Package Label- Principal Display Panel

250 mL NDC: 78755-002-03

Package Label- Principal Display Panel

500 mL NDC: 78755-002-04

Package Label- Principal Display Panel

1000 mL NDC: 78755-002-05

Package Label- Principal Display Panel

3780 mL NDC: 78755-002-06